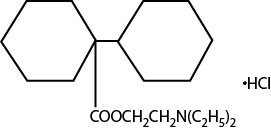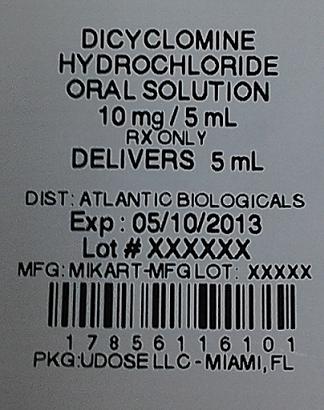 DRUG LABEL: dicyclomine hydrochloride
NDC: 17856-1161 | Form: SOLUTION
Manufacturer: Atlantic Biologicals Corps
Category: prescription | Type: HUMAN PRESCRIPTION DRUG LABEL
Date: 20160829

ACTIVE INGREDIENTS: DICYCLOMINE HYDROCHLORIDE 10 mg/5 mL
INACTIVE INGREDIENTS: D&C RED NO. 33; FD&C BLUE NO. 1; FD&C RED NO. 40; FD&C YELLOW NO. 6; GLYCERIN; METHYLPARABEN; PROPYLENE GLYCOL; PROPYLPARABEN; SORBITOL; SUCROSE; WATER

DESCRIPTION

Dicyclomine hydrochloride oral solution is an antispasmodic and anticholinergic (antimuscarinic) agent. Each 5 mL (teaspoonful) of Dicyclomine HCl Oral Solution USP for oral administration contains:

Dicyclomine HCl …………………………. 10 mg

Also contains glycerin, methylparaben, propylene glycol, propylparaben, purified water, sorbitol solution, sucrose, with D&C Red #33, FD&C Blue #1, FD&C Red #40, FD&C Yellow #6 as coloring, and natural and artificial berry flavoring.

Chemically, dicyclomine hydrochloride is [bicyclohexyl]-1-carboxylic acid, 2-(diethylamino) ethyl ester, hydrochloride. Dicyclomine hydrochloride occurs as a fine, white, crystalline, practically odorless powder with a bitter taste. It is soluble in water, freely soluble in alcohol and chloroform, and very slightly soluble in ether. Its structural formula is as follows:

C H NO • HCl M.W. 345.9519352

CLINICAL PHARMACOLOGY

Dicyclomine relieves smooth muscle spasm of the gastrointestinal tract. Animal studies indicate that this action is achieved via a dual mechanism: (1) a specific anticholinergic effect (antimuscarinic) at the acetylcholine-receptor sites with approximately 1/8 the milligram potency of atropine (, guinea pig ileum): and (2) a direct effect upon smooth muscle (musculotropic) as evidenced by dicyclomine’s antagonism of bradykinin-and histamine-induced spasms of the isolated guinea pig ileum. Atropine did not affect responses to these two agonists. studies in cats and dogs showed dicyclomine to be equally potent against acetylcholine (ACh)- or barium chloride (BaCl)-induced intestinal spasm while atropine was at least 200 times more potent against effects of ACh than BaCl . Tests for mydriatic effects in mice showed that dicyclomine was approximately 1/500 as potent as atropine; antisialagogue tests in rabbits showed dicyclomine to be 1/300 as potent as atropine. in vitro In vivo22

In man, dicyclomine is rapidly absorbed after oral administration, reaching peak values within 60-90 minutes. The principal route of elimination is via the urine (79.5% of the dose). Excretion also occurs in the feces, but to a lesser extent (8.4%). Mean half-life of plasma elimination in one study was determined to be approximately 1.8 hours when plasma concentrations were measured for 9 hours after a single dose. In subsequent studies, plasma concentrations were followed for up to 24 hours after a single dose, showing a secondary phase of elimination with a somewhat longer half-life. Mean volume of distribution for a 20 mg oral dose is approximately 3.65 L/kg suggesting extensive distribution in tissues.

In controlled clinical trials involving over 100 patients who received drug, 82% of patients treated for functional bowel/irritable bowel syndrome with dicyclomine hydrochloride at initial doses of 160 mg daily (40 mg q.i.d.) demonstrated a favorable clinical response compared with 55% treated with placebo. (P<0.05). In these trials, most of the side effects were typically anticholinergic in nature (see table) and were reported by 61% of the patients.

Side Effect | (40 mg q.i.d.) %; Dicyclomine Hydrochloride | %; Placebo
Dry Mouth | 33 | 5
Dizziness | 29 | 2
Blurred Vision | 27 | 2
Nausea | 14 | 6
Lightheadedness | 11 | 3
Drowsiness | 9 | 1
Weakness | 7 | 1
Nervousness | 6 | 2

Nine percent (9%) of patients were discontinued from the drug because of one or more of these side effects (compared with 2% in the placebo group). In 41% of the patients with side effects, side effects disappeared or were tolerated at the 160 mg daily dose without reduction. A dose reduction from 160 mg daily to an average daily dose of 90 mg was required in 46% of the patients with side effects who then continued to experience a favorable clinical response; their side effects either disappeared or were tolerated. (See .) ADVERSE REACTIONS

INDICATIONS AND USAGE

Dicyclomine hydrochloride oral solution is indicated for the treatment of functional bowel/irritable bowel syndrome.

CONTRAINDICATIONS

1. Obstructive uropathy
2. Obstructive disease of the gastrointestinal tract
3. Severe ulcerative colitis (see) PRECAUTIONS
4. Reflux esophagitis
5. Unstable cardiovascular status in acute hemorrhage
6. Glaucoma
7. Myasthenia gravis
8. Evidence of prior hypersensitivity to dicyclomine hydrochloride or other ingredients in this formulation
9. Infants less than 6 months of age (see and : .) WARNINGSPRECAUTIONSInformation for Patients
10. Nursing Mothers (see and : .) WARNINGSPRECAUTIONSInformation for Patients

WARNINGS

In the presence of a high environmental temperature, heat prostration can occur with drug use (fever and heat stroke due to decreased sweating). If symptoms occur, the drug should be discontinued and supportive measures instituted.

Diarrhea may be an early symptom of incomplete intestinal obstruction, especially in patients with ileostomy or colostomy. In this instance, treatment with this drug would be inappropriate and possibly harmful.

Dicyclomine hydrochloride oral solution may produce drowsiness or blurred vision. The patient should be warned not to engage in activities requiring mental alertness, such as operating a motor vehicle or other machinery or performing hazardous work while taking this drug.

Psychosis has been reported in sensitive individuals given anticholinergic drugs. CNS signs and symptoms include confusion, disorientation, short-term memory loss, hallucinations, dysarthria, ataxia, coma, euphoria, decreased anxiety, fatigue, insomnia, agitation and mannerisms, and inappropriate affect.

These CNS signs and symptoms usually resolve within 12 to 24 hours after discontinuation of the drug.

There are reports that administration of dicyclomine hydrochloride oral soution to infants has been followed by serious respiratory symptoms (dyspnea, shortness of breath, breathlessness, respiratory collapse, apnea, asphyxia), seizures, syncope, pulse rate fluctuations, muscular hypotonia, and coma. Death has been reported. No causal relationship between these effects observed in infants and dicyclomine administration has been established. DICYCLOMINE HYDROCHLORIDE ORAL SOLUTION IS CONTRAINDICATED IN INFANTS LESS THAN 6 MONTHS OF AGE AND IN NURSING MOTHERS. (See and :). CONTRAINDICATIONSPRECAUTIONSand Nursing Mothers Pediatric Use

Safety and efficacy of dicyclomine hydrochloride in pediatric patients have not been established.

PRECAUTIONS

General

Use with caution in patients with:

1. Autonomic neuropathy
2. Hepatic or renal disease
3. Ulcerative colitis-large doses may suppress intestinal motility to the point of producing a paralytic ileus and the use of this drug may precipitate or aggravate the serious complication of toxic megacolon (see) CONTRAINDICATIONS
4. Hyperthyroidism
5. Hypertension
6. Coronary heart disease
7. Congestive heart failure
8. Cardiac tachyarrhythmia
9. Hiatal hernia (see : reflux esophagitis) CONTRAINDICATIONS
10. Known or suspected prostatic hypertrophy.

Investigate any tachycardia before administration of dicyclomine hydrochloride, since it may increase the heart rate.

With overdosage, a curare-like action may occur (i.e., neuromuscular blockade leading to muscular weakness and possible paralysis).

Information for Patients

Dicyclomine hydrochloride may produce drowsiness or blurred vision. The patient should be warned not to engage in activities requiring mental alertness, such as operating a motor vehicle or other machinery or to perform hazardous work while taking this drug.

Dicyclomine hydrochloride is contraindicated in infants less than 6 months of age and in nursing mothers. (See , , and :). CONTRAINDICATIONSWARNINGSPRECAUTIONSand Nursing Mothers Pediatric Use

In the presence of a high environmental temperature, heat prostration can occur with drug use (fever and heat stroke due to decreased sweating). If symptoms occur, the drug should be discontinued and a physician contacted.

Drug Interactions

The following agents may increase certain actions or side effects of anticholinergic drugs: amantadine, antiarrhythmic agents of Class I (e.g., quinidine), antihistamines, antipsychotic agents (e.g., phenothiazines), benzodiazepines, MAO inhibitors, narcotic analgesics (e.g., meperidine), nitrates and nitrites, sympathomimetic agents, tricyclic antidepressants, and other drugs having anticholinergic activity.

Anticholinergics antagonize the effects of antiglaucoma agents. Anticholinergic drugs in the presence of increased intraocular pressure may be hazardous when taken concurrently with agents such as corticosteroids. (See also .) CONTRAINDICATIONS

Anticholinergic agents may affect gastrointestinal absorption of various drugs, such as slowly dissolving dosage forms of digoxin; increased serum digoxin concentrations may result. Anticholinergic drugs may antagonize the effects of the drugs that alter gastrointestinal motility, such as metoclopramide. Because antacids may interfere with the absorption of anticholinergic agents, simultaneous use of these drugs should be avoided.

The inhibiting effects of anticholinergic drugs on gastric hydrochloric acid secretion are antagonized by agents used to treat achlorhydria and those used to test gastric secretion.

Carcinogenesis, Mutagenesis, Impairment of Fertility

There are no known human data on long-term potential for carcinogenicity or mutagenicity.

Long-term studies in animals to determine carcinogenic potential are not known to have been conducted.

In studies in rats at doses of up to 100 mg/kg/day, dicyclomine hydrochloride produced no deleterious effects on breeding, conception, or parturition.

Teratogenic Effects

Pregnancy Category B

Reproduction studies have been performed in rats and rabbits at doses up to 33 times the maximum recommended human dose based on 160 mg/day (3 mg/kg) and have revealed no evidence of impaired fertility or harm to the fetus due to dicyclomine. Epidemiologic studies in pregnant women with products containing dicyclomine hydrochloride (at doses up to 40 mg/day) have not shown that dicyclomine increases the risk of fetal abnormalities if administered during the first trimester of pregnancy. There are, however, no adequate and well-controlled studies in pregnant women at the recommended doses (80-l60 mg/day). Because animal reproduction studies are not always predictive of human response, dicyclomine hydrochloride as indicated for functional bowel/irritable bowel syndrome should be used during pregnancy only if clearly needed.

Nursing Mothers

Since dicyclomine hydrochloride has been reported to be excreted in human milk, DICYCLOMINE HYDROCHLORIDE IS CONTRAINDICATED IN NURSING MOTHERS. (See , , : and) CONTRAINDICATIONSWARNINGSPRECAUTIONSPediatric Use. ADVERSE REACTIONS

Pediatric Use

(See , , and :). DICYCLOMINE HYDROCHLORIDE IS CONTRAINDICATED IN INFANTS LESS THAN 6 MONTHS OF AGE. CONTRAINDICATIONSWARNINGSPRECAUTIONSNursing Mothers

Safety and effectiveness in pediatric patients have not been established.

Geriatric Use

Clinical studies of dicyclomine hydrochloride oral solution did not include sufficient numbers of subjects aged 65 and over to determine whether they respond differently from younger subjects. Other reported clinical experience has not identified differences in responses between the elderly and younger patients. In general, dose selection for an elderly patient should be cautious, usually starting at the low end of the dosing range, reflecting the greater frequency of decreased hepatic, renal, or cardiac function, and of concomitant disease or other drug therapy. (See) DOSAGE AND ADMINISTRATION

This drug is known to be substantially excreted by the kidney, and the risk of toxic reactions to this drug may be greater in patients with impaired renal function. Because elderly patients are more likely to have decreased renal function, care should be taken in dose selection, and it may be useful to monitor renal function.

ADVERSE REACTIONS

Controlled clinical trials have provided frequency information for reported adverse effects of dicyclomine hydrochloride listed in a decreasing order of frequency. (See .) CLINICAL PHARMACOLOGY

Not all of the following adverse reactions have been reported with dicyclomine hydrochloride. Adverse reactions are included here that have been reported for pharmacologically similar drugs with anticholinergic/antispasmodic action.

dry mouth, nausea, vomiting, constipation. bloated feeling, abdominal pain, taste loss, anorexia. Gastrointestinal :

dizziness, lightheadedness, tingling, headache, drowsiness, weakness, nervousness, numbness, mental confusion and/or excitement (especially in elderly persons), dyskinesia, lethargy, syncope, speech disturbance, insomnia. Central Nervous System :

blurred vision, diplopia, mydriasis, cycloplegia, increased ocular tension Ophthalmologic:

rash, urticaria, itching, and other dermal manifestations; severe allergic reaction or drug idiosyncrasies including anaphylaxis. Dermatologic/Allergic:

urinary hesitancy, urinary retention Genitourinary:

tachycardia. palpitations Cardiovascular:

Dyspnea, apnea, asphyxia (see) Respiratory: WARNINGS

decreased sweating, nasal stuffiness or congestion, sneezing, throat congestion, impotence, suppression of lactation (see :) Other: PRECAUTIONSNursing Mothers

DRUG ABUSE AND DEPENDENCE

Abuse of and/or dependence on dicyclomine for anticholinergic effects have been rarely reported.

OVERDOSAGE

Signs and Symptoms

The signs and symptoms of overdosage are headache; nausea; vomiting; blurred vision; dilated pupils; hot, dry skin; dizziness; dryness of the mouth; difficulty in swallowing; and CNS stimulation. A curare-like action may occur (i.e., neuromuscular blockade leading to muscular weakness and possible paralysis).

A 37-year-old female reported numbness on the left side, cold fingertips, blurred vision, abdominal and flank pain, decreased appetite, dry mouth, and nervousness following ingestion of 320 mg daily (four 20 mg tablets QID) for four days. These events resolved after discontinuing the dicyclomine.

Oral LD50

The acute oral LD of the drug is 625 mg/kg in mice.50

Minimum Human Lethal Dose/Maximum Human Dose Recorded

The amount of drug in a single dose that is ordinarily associated with symptoms of overdosage or that is likely to be life threatening, has not been defined. The maximum human oral dose recorded was 600 mg by mouth in a 10-month-old child and approximately 1500 mg in an adult, each of whom survived.

In three of the infants who died following administration of dicyclomine hydrochloride (see), the blood concentrations of drug were 200, 220, and 505 ng/mL, respectively. WARNINGS

Dialysis

It is not known if dicyclomine hydrochoride is dialyzable.

Treatment

Treatment should consist of gastric lavage, emetics, and activated charcoal. Sedatives (e.g., short-acting barbiturates, benzodiazepines) may be used for management of overt signs of excitement. If indicated, an appropriate parenteral cholinergic agent may be used as an antidote.

DOSAGE AND ADMINISTRATION

DOSAGE MUST BE ADJUSTED TO INDIVIDUAL PATIENT NEEDS. (See .) CLINICAL PHARMACOLOGY

Adults-Oral

The only oral dose clearly shown to be effective is 160 mg per day (in 4 equally divided doses). Since this dose is associated with a significant incidence of side effects, it is prudent to begin with 80 mg per day (in 4 equally divided doses). Depending upon the patient’s response during the first week of therapy, the dose should be increased to 160 mg per day unless side effects limit dosage escalation.

If efficacy is not achieved within 2 weeks or side effects require doses below 80 mg per day, the drug should be discontinued. Documented safety data are not available for doses above 80 mg daily for periods longer than 2 weeks.

Elderly

In general, dose selection for an elderly patient should be cautious, usually starting at the low end of the dosing range, reflecting the greater frequency of decreased hepatic, renal, or cardiac function, and of concomitant disease or other drug therapy. (See :) PRECAUTIONSGeriatric Use

Manufactured by:

MIKART, INC.

Atlanta, GA 30318

Code 814Z00

Rev 03/08